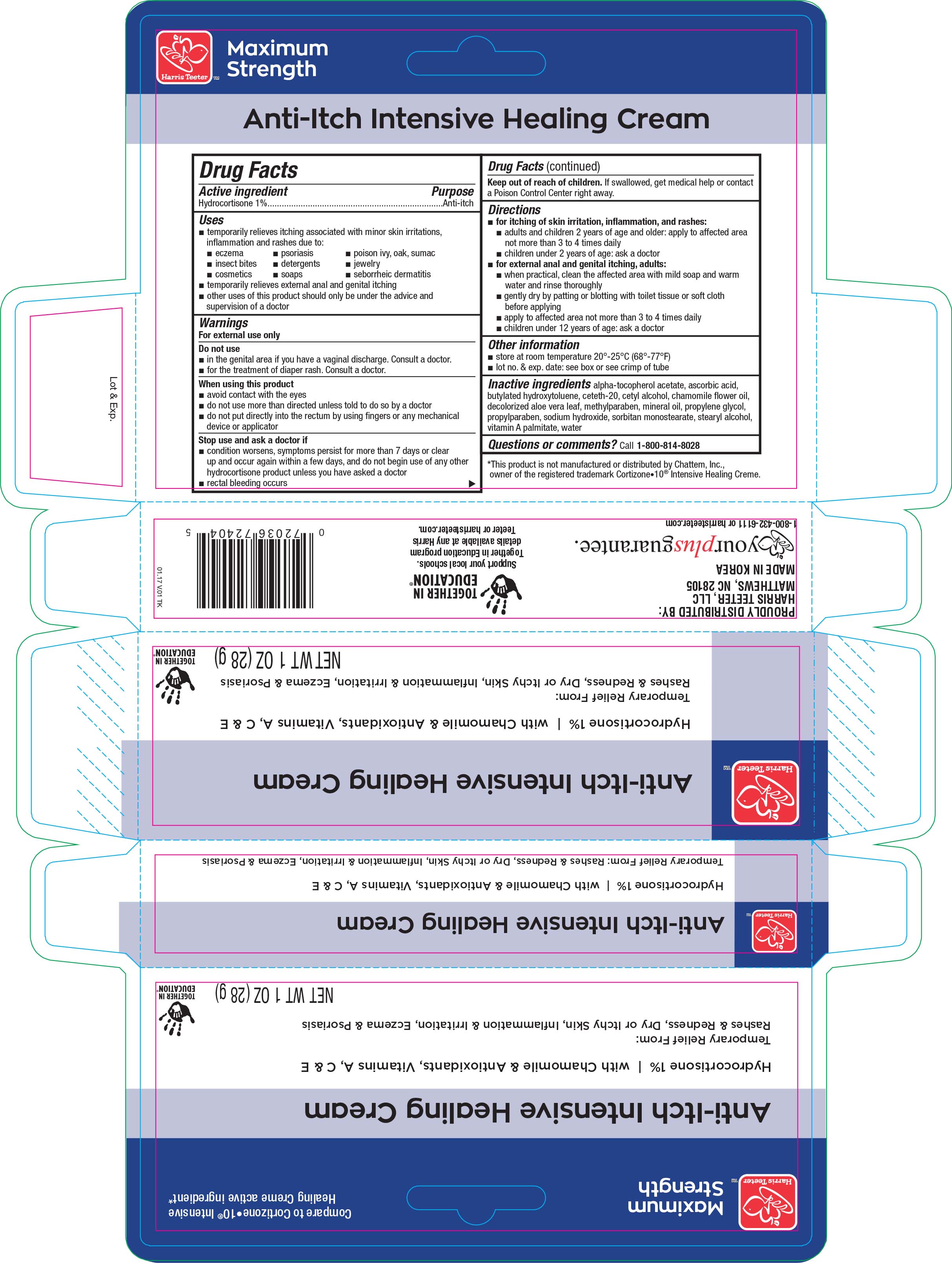 DRUG LABEL: Harris Teeter Anti-Itch Intensive Healing
NDC: 72036-404 | Form: CREAM
Manufacturer: Harris Teeter
Category: otc | Type: HUMAN OTC DRUG LABEL
Date: 20170420

ACTIVE INGREDIENTS: HYDROCORTISONE 1 g/100 g
INACTIVE INGREDIENTS: ALPHA-TOCOPHEROL ACETATE; ASCORBIC ACID; BUTYLATED HYDROXYTOLUENE; CETETH-20; CETYL ALCOHOL; CHAMOMILE FLOWER OIL; ALOE VERA LEAF; METHYLPARABEN; MINERAL OIL; PROPYLENE GLYCOL; PROPYLPARABEN; SODIUM HYDROXIDE; SORBITAN MONOSTEARATE; STEARYL ALCOHOL; VITAMIN A PALMITATE; WATER

Active ingredient Purpose

Hydrocortisone 1%........................................Anti-itch

Uses

- temporarily relieves itching associated with minor skin irritations, inflammation and rashes due to:
- eczema
- insect bites
- cosmetics
- psoriasis
- detergents
- soaps
- poison ivy, oak, sumac
- jewelry
- seborrheic dermatitis
- temporarily relieves external anal and genital itching
- other uses of this product should only be under the advice and supervison of a doctor

Warnings

For external use only

Do not use

- in the genital area if you have a vaginal discharge. Consult a doctor.
- for the treatment of diaper rash. Consult a doctor.

When using this product

- avoid contact with the eyes
- do not use more than directed unless told to do so by a doctor
- do not pull directly into the rectum by using fingers or any mechanical device or applicator

Stop use and ask a doctor if

- condition worsens, symptoms persist for more than 7 days or clear up and occur again within a few days, and do not begin use of any other

hydrocortisone product unless you have asked a doctor.

- rectal bleeding occurs

Keep out of reach of children. If swallowed, get medical help or contact a Poison Control Center right away.

Directions

- for itching of skin irriation, inflammation, and rashes:
- adults and children 2 years of age and older: apply to affected area not more than 3 to 4 times daily
- children under 2 years of age: ask a doctor
- for external anal and genital itching, adults:
- when practical, clean the affected area with mild soap and warm water and rinse thoroughly
- gently dry by patting or blotting with toilet tissue or soft cloth before applying
- apply to affected area not more than 3 to 4 times daily
- children under 12 years of age: ask a doctor

Other information

- store at room temperature 20°-25°C (68°-77°F)
- lot no. & exp. date: see box or see crimp of tube

Inactive ingredients

alpha-tocopherol acetate, ascorbig acid, butylated hydroxtoluene, ceteth-20, cetyl alcohol, chamomile flower oil, decolorized aloe vera leaf,

methylparaben, mineral oil, propylene glycol, propylparaben, sodium hydroxide, sorbitan monostearate, stearyl alcohol, vitamin A palmitate,

water

DOSAGE AND ADMINISTRATION

Distributed by:

Harris Teeter, LLC

Matthews, NC 28105

Made in Korea